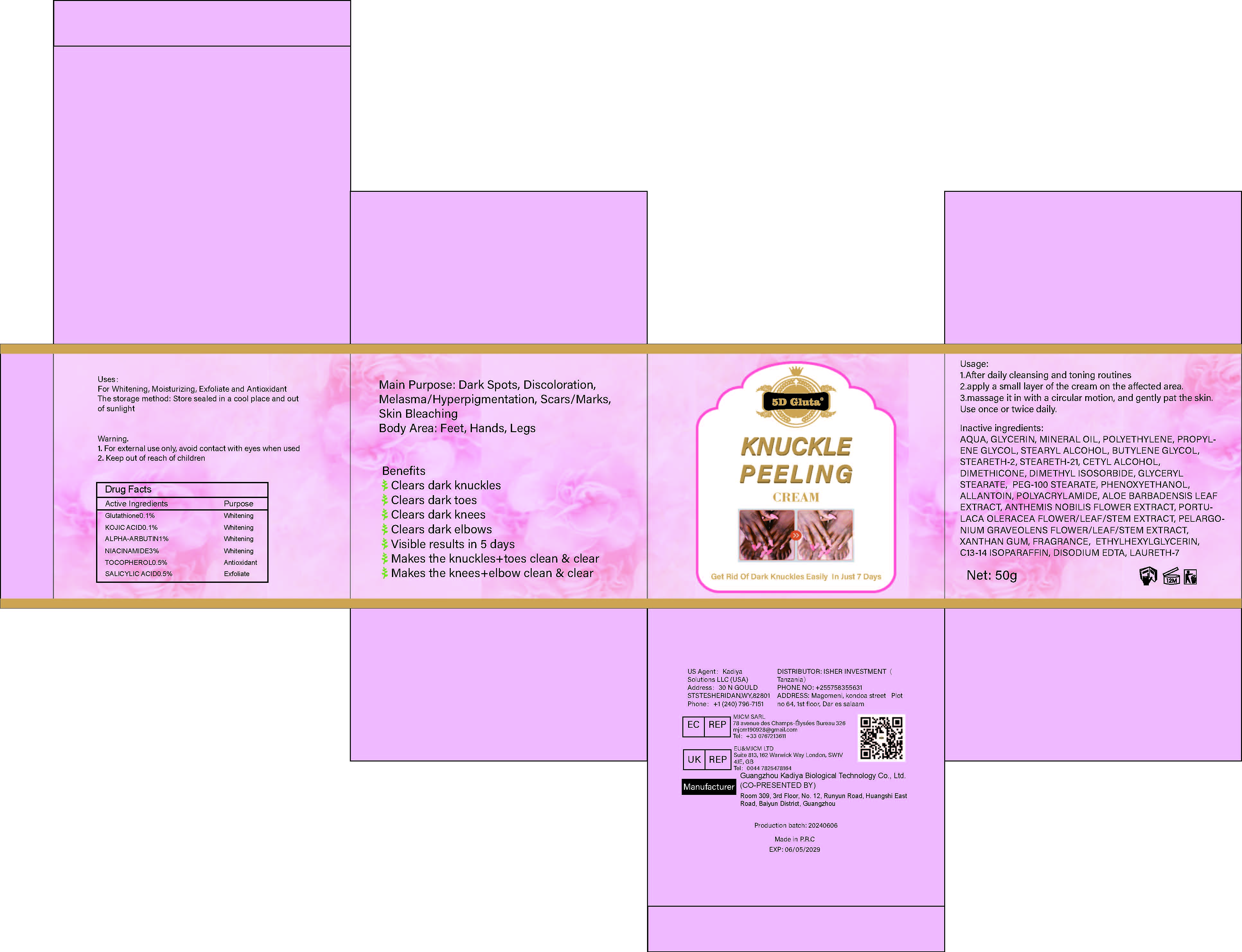 DRUG LABEL: KnucklePeelingCream
NDC: 84423-063 | Form: CREAM, AUGMENTED
Manufacturer: Guangzhou Kadiya Biotechnology Co., Ltd.
Category: otc | Type: HUMAN OTC DRUG LABEL
Date: 20241217

ACTIVE INGREDIENTS: KOJIC ACID 0.05 g/50 g; SALICYLIC ACID 0.25 g/50 g; TOCOPHEROL 0.25 g/50 g; GLUTATHIONE 0.05 g/50 g; NIACINAMIDE 1.5 g/50 g; ALPHA-ARBUTIN 0.5 g/50 g
INACTIVE INGREDIENTS: PROPYLENE GLYCOL; AQUA; STEARYL ALCOHOL; PEG-100 STEARATE; ALLANTOIN; LAURETH-7; STEARETH-21; DIMETHICONE 1000; STEARETH-2; PHENOXYETHANOL; CHAMAEMELUM NOBILE FLOWER; XANTHAN GUM; EDETATE DISODIUM; GLYCERYL STEARATE; PELARGONIUM GRAVEOLENS FLOWERING TOP; POLYETHYLENE; GLYCERIN; MINERAL OIL; CETYL ALCOHOL; BUTYLENE GLYCOL; C13-14 ISOPARAFFIN; DIMETHYL ISOSORBIDE; POLYACRYLAMIDE (10000 MW); ALOE BARBADENSIS LEAF JUICE; PURSLANE; ETHYLHEXYLGLYCERIN

PURPOSE

For Whitening, Moisturizing，Exfoliate and Antioxidant

INACTIVE INGREDIENT

AQUA，GLYCERIN，MINERAL OIL，POLYETHYLENE，PROPYLENE GLYCOL，STEARYL ALCOHOL，BUTYLENE GLYCOL，STEARETH-2，STEARETH-21，CETYL ALCOHOL，DIMETHICONE，DIMETHYL ISOSORBIDE，GLYCERYL STEARATE， PEG-100 STEARATE，PHENOXYETHANOL，ALLANTOIN，POLYACRYLAMIDE，ALOE BARBADENSIS LEAF EXTRACT，ANTHEMIS NOBILIS FLOWER EXTRACT，PORTULACA OLERACEA FLOWER/LEAF/STEM EXTRACT，PELARGONIUM GRAVEOLENS FLOWER/LEAF/STEM EXTRACT，XANTHAN GUM，FRAGRANCE， ETHYLHEXYLGLYCERIN，C13-14 ISOPARAFFIN，DISODIUM EDTA，LAURETH-7

WARNINGS

1、For external use only, avoid contact with eyes when used
2、Keep out of reach of children

INDICATIONS AND USAGE

Dark Spots, Discoloration, Melasma/Hyperpigmentation, Scars/Marks, Skin Bleaching

DOSAGE AND ADMINISTRATION

Body Area: Feet, Hands, Legs

KEEP OUT OF REACH OF CHILDREN SECTION

Active Ingredients Purpose
Glutathione0.1% Whitening
KOJIC ACID0.1% Whitening
ALPHA-ARBUTIN1% Whitening
NIACINAMIDE3% Whitening
TOCOPHEROL0.5% Antioxidant
SALICYLIC ACID0.5 Exfoliate

PACKAGE LABEL

Active Ingredients Purpose
Glutathione0.1% Whitening
KOJIC ACID0.1% Whitening
ALPHA-ARBUTIN1% Whitening
NIACINAMIDE3% Whitening
TOCOPHEROL0.5% Antioxidant
SALICYLIC ACID0.5 Exfoliate

Uses：
For Whitening, Moisturizing，Exfoliate and Antioxidant
The storage method：
Store sealed in a cool place and out of sunlight

Warning.
1、For external use only, avoid contact with eyes when used
2、Keep out of reach of children

Inactive ingredients：
AQUA，GLYCERIN，MINERAL OIL，POLYETHYLENE，PROPYLENE GLYCOL，STEARYL ALCOHOL，BUTYLENE GLYCOL，STEARETH-2，STEARETH-21，CETYL ALCOHOL，DIMETHICONE，DIMETHYL ISOSORBIDE，GLYCERYL STEARATE， PEG-100 STEARATE，PHENOXYETHANOL，ALLANTOIN，POLYACRYLAMIDE，ALOE BARBADENSIS LEAF EXTRACT，ANTHEMIS NOBILIS FLOWER EXTRACT，PORTULACA OLERACEA FLOWER/LEAF/STEM EXTRACT，PELARGONIUM GRAVEOLENS FLOWER/LEAF/STEM EXTRACT，XANTHAN GUM，FRAGRANCE， ETHYLHEXYLGLYCERIN，C13-14 ISOPARAFFIN，DISODIUM EDTA，LAURETH-7